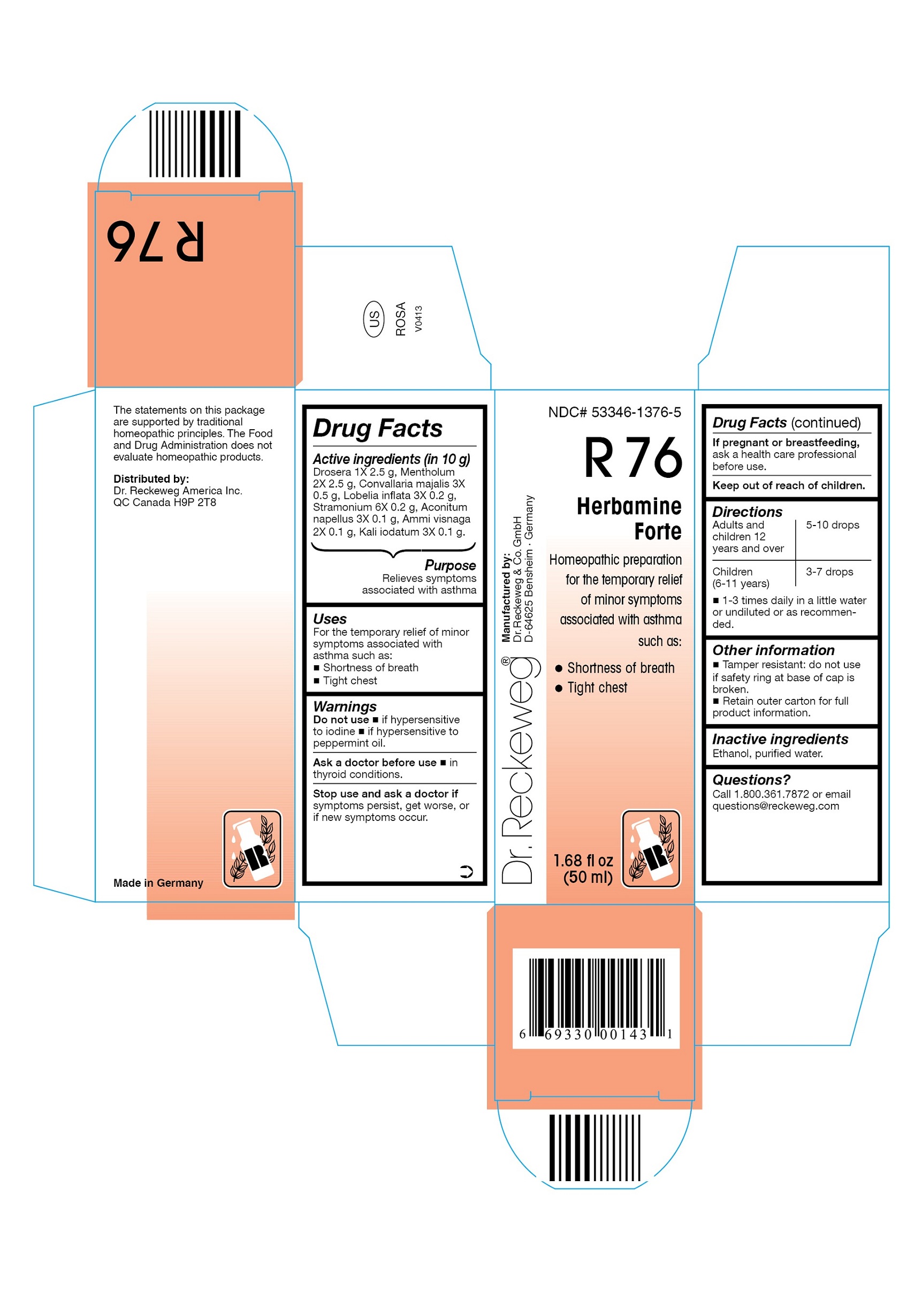 DRUG LABEL: DR. RECKEWEG R76 Herbamine Forte
NDC: 53346-1376 | Form: LIQUID
Manufacturer: PHARMAZEUTISCHE FABRIK DR. RECKEWEG & CO
Category: homeopathic | Type: HUMAN OTC DRUG LABEL
Date: 20130403

ACTIVE INGREDIENTS: DROSERA ROTUNDIFOLIA 1 [hp_X]/50 mL; MENTHOL 2 [hp_X]/50 mL; CONVALLARIA MAJALIS 3 [hp_X]/50 mL; LOBELIA INFLATA 3 [hp_X]/50 mL; DATURA STRAMONIUM 6 [hp_X]/50 mL; ACONITUM NAPELLUS 3 [hp_X]/50 mL; AMMI VISNAGA FRUIT 2 [hp_X]/50 mL; POTASSIUM IODIDE 3 [hp_X]/50 mL
INACTIVE INGREDIENTS: ALCOHOL; WATER

DR. RECKEWEG R76 Herbamine Forte

Active ingredients

Drosera 1X 2.5 g, Mentholum 2X 2.5 g, Convallaria majalis 3X 0.5 g, Lobelia inflata 3X 0.2 g, Stramonium 6X 0.2 g, Aconitum napellus 3X 0.1 g, Ammi visnaga 2X 0.1 g, Kali iodatum 3X 0.1 g in 10 g.

Purpose

Relieves symptoms associated with asthma

Uses

For the temporary relief of minor symptoms associated with asthma such as:

- Shortness of breath
- Tight chest

Warnings

Do not use

- if hypersensitive to iodine.
- if hypersensitive to peppermint oil.

Ask a doctor before use

- in thyroid conditions.

Stop use and ask a doctor if symptoms persist, get worse, or if new symptoms occur.

PREGNANCY OR BREAST FEEDING

If pregnant or breastfeeding, ask a health care professional before use.

Keep out of reach of children.

Directions

Adults and children ≥ 12 years 5-10 drops; children (6-11 years) 3-7 drops 1-3 times daily in a little water or undiluted or as recommended.

Other information

- Tamper resistant: Do not use if safety ring at base of cap is broken.
- Retain outer carton for full product information.

Inactive ingredients

Ethanol, purified water.

Questions?
Call 1-800-361-7872 or email questions@reckeweg.com

PACKAGE LABEL

NDC# 53346-1376-5

Dr. Reckeweg R76 Herbamine Forte

Homeopathic preparation for the temporary relief of minor symptoms associated with asthma such as:

- Shortness of breath
- Tight chest

Manufactured by:

Dr. Reckeweg Co. GmbH

D-64625 Bensheim

Germany

1.68 fl oz
(50 ml)